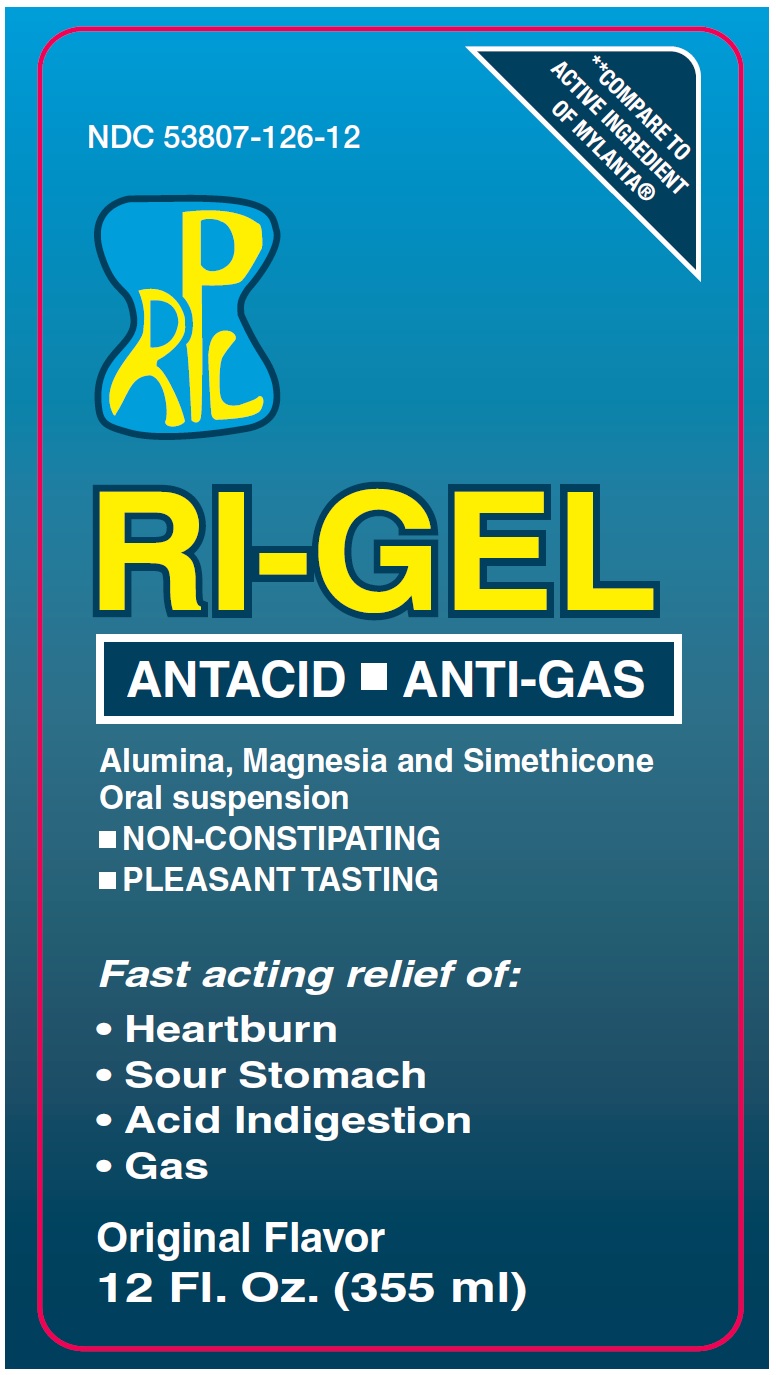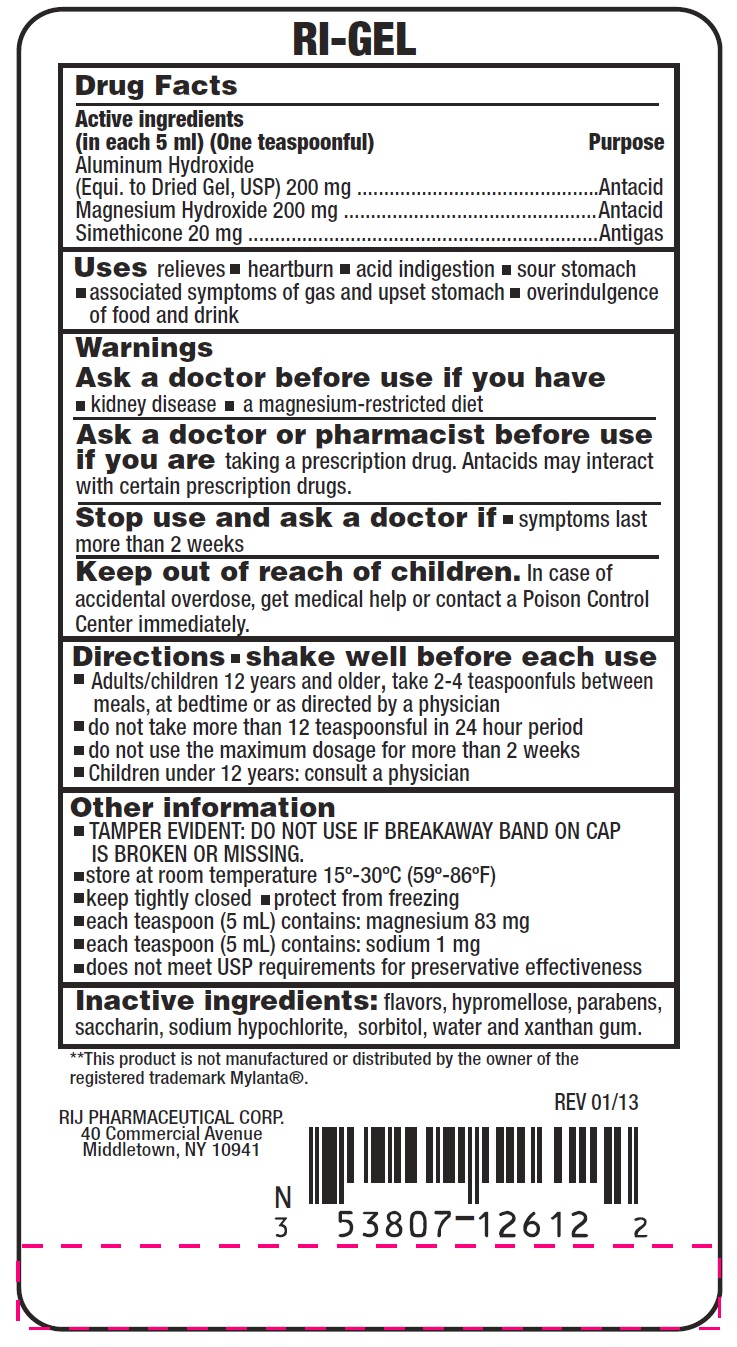 DRUG LABEL: antacid
NDC: 53807-126 | Form: LIQUID
Manufacturer: Rij Pharmaceutical Corporation
Category: otc | Type: HUMAN OTC DRUG LABEL
Date: 20180430

ACTIVE INGREDIENTS: ALUMINUM HYDROXIDE 200 mg/5 mL; MAGNESIUM HYDROXIDE 200 mg/5 mL; DIMETHICONE 20 mg/5 mL
INACTIVE INGREDIENTS: HYPROMELLOSES; BUTYLPARABEN;  SACCHARIN; SODIUM HYPOCHLORITE; SORBITOL; PROPYLPARABEN; WATER; XANTHAN GUM; LEMON OIL

Drug Facts

Active ingredients (in each 5 mL = 1 teaspoonful)

Aluminum hydroxide (Equi. To Dried Gel, USP) 200 mg

Magnesium hydroxide 200 mg

Simethicone 20 mg

Purpose

Antacid

Antigas

Uses

relieves

- heartburn
- acid indigestion
- sour stomach
- associated symptoms of gas and upset stomach
- overindulgence of food and drink

Warnings

Ask a doctor before use if you have

- kidney disease
- a magnesium-restricted diet

Ask a doctor or pharmacist before use if you are

taking a prescription drug. Antacids may interact with certain prescription drugs.

Stop use and ask a doctor if

- symptoms last for more than 2 weeks

Keep out of reach of children.

In case of accidental overdose, get medical help or contact a Poison Control Center immediately.

Directions

- shake well before each use
- Adults/children 12 years and older, take 2 - 4 teaspoonsful between meals, at bedtime or as directed by a physician
- do not take more than 12 teaspoonsful in 24
- do not use the maximum dosage for more than 2 weeks
- children under 12 years: consult a physician

Other information

- TAMPER EVIDENT: DO NOT USE IF BREAKAWAY BAND ON CAP IS BROKEN OR MISSING
- Store at room temperature 15º - 30ºC (59º - 86ºF)
- keep tightly closed
- protect from freezing
- each teaspoon (5 mL) contains: magnesium 83 mg
- each teaspoon (5 mL) contains: sodium 1 mg
- does not meet USP requirements for preservative effectiveness

Inactive ingredients

flavors, hypromellose, parabens, saccharin, sodium hypochlorite, sorbitol, water and xanthan gum